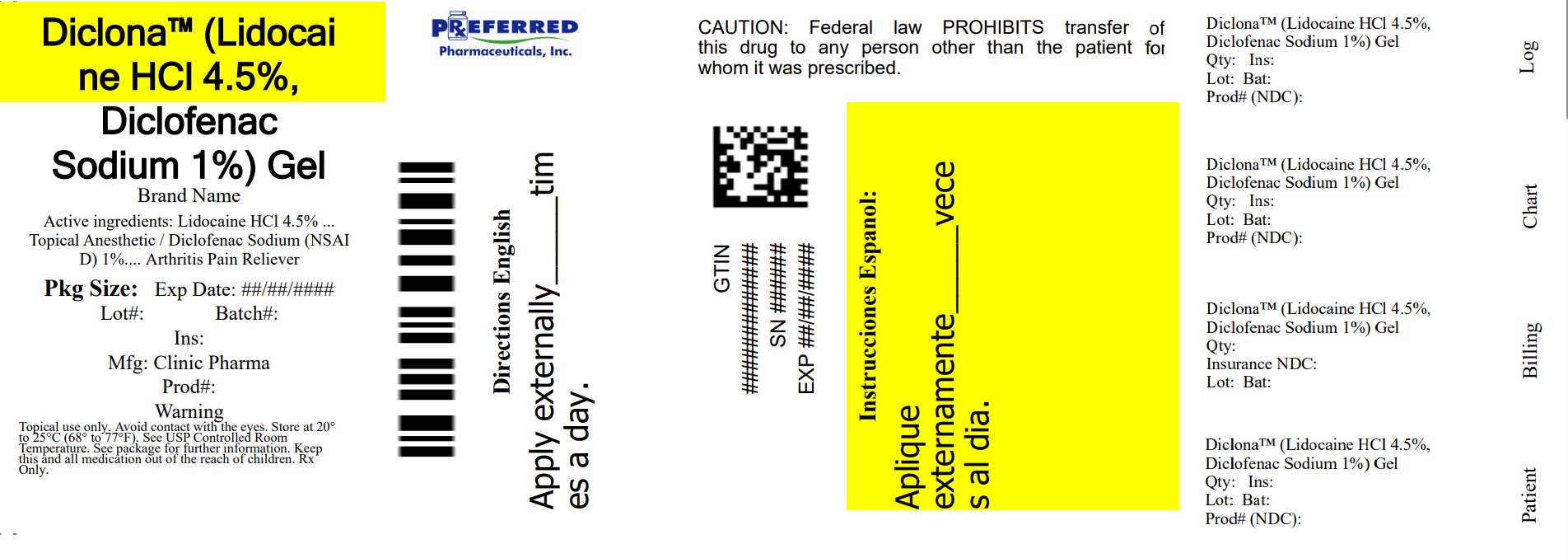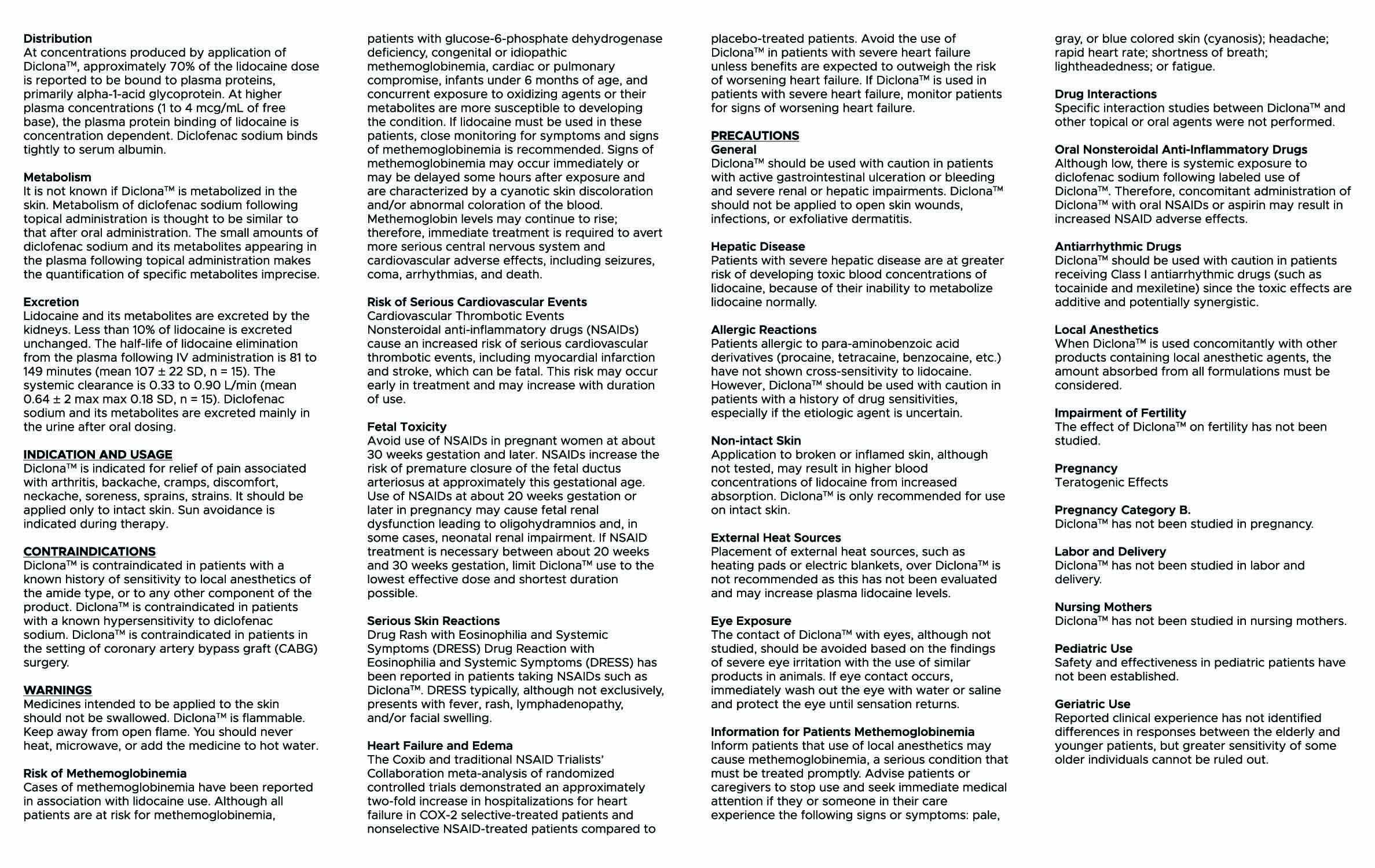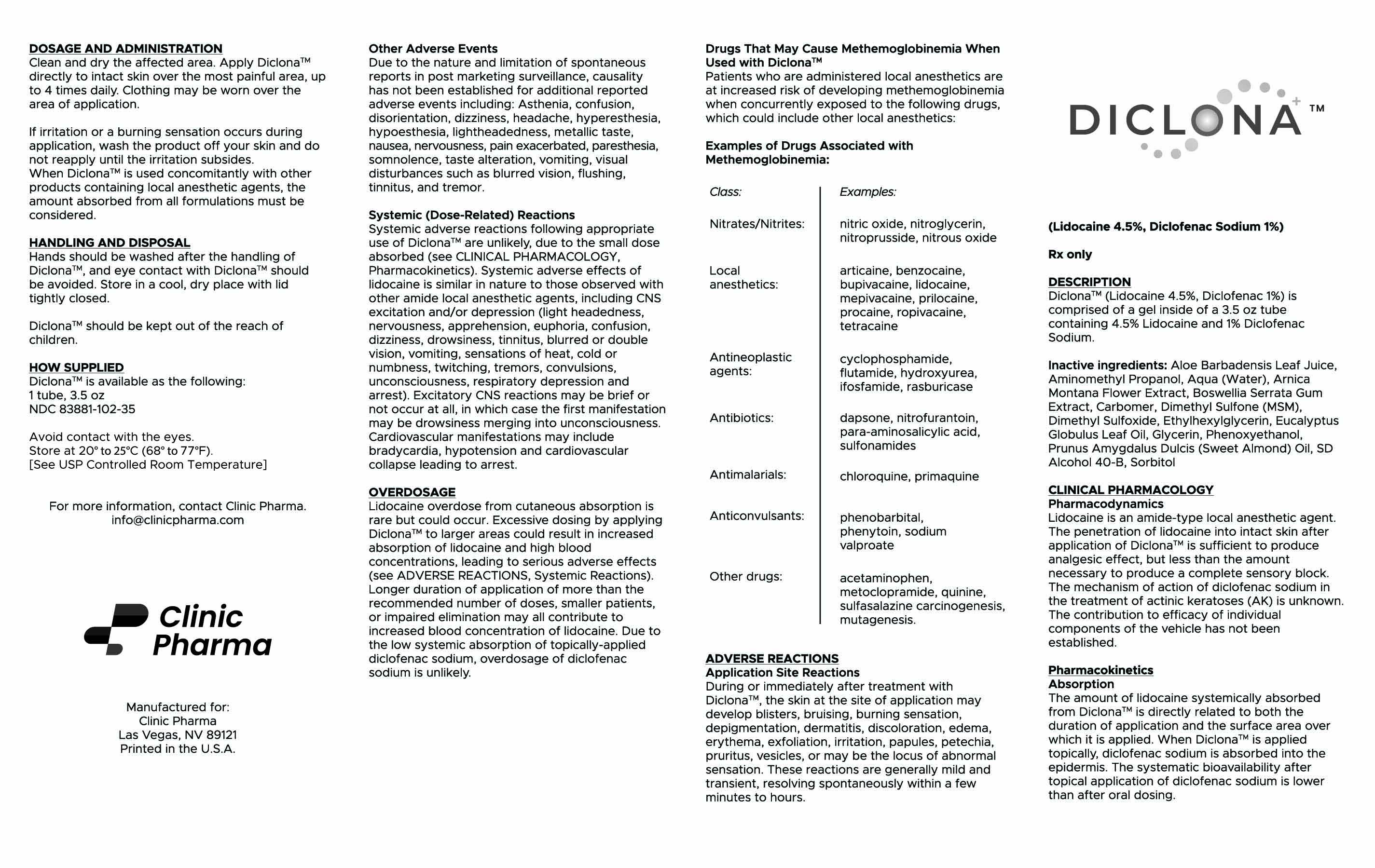 DRUG LABEL: Diclona
NDC: 68788-4013 | Form: GEL
Manufacturer: Preferred Pharmaceuticals Inc.
Category: prescription | Type: HUMAN PRESCRIPTION DRUG LABEL
Date: 20250905

ACTIVE INGREDIENTS: DICLOFENAC SODIUM 0.01 g/1 g; LIDOCAINE 0.045 g/1 g
INACTIVE INGREDIENTS: PHENOXYETHANOL; ARNICA MONTANA FLOWER; WATER; CARBOMER HOMOPOLYMER, UNSPECIFIED TYPE; ETHYLHEXYLGLYCERIN; SORBITOL; ALCOHOL; ALOE VERA LEAF; DIMETHYL SULFOXIDE; EUCALYPTUS OIL; DIMETHYL SULFONE; ALMOND; INDIAN FRANKINCENSE

Diclona™

Diclona

(Lidocaine 4.5%, Diclofenac Sodium 1%)

Rx only - Gel

DESCRIPTION

Diclona™ is comprised of a gel inside of a 3.5oz tube containing 4.5% Lidocaine and 1% Diclofenac Sodium.

Inactive ingredients: Aloe Barbadensis (Aloe Vera) Leaf Juice, Arnica Montana Flower Extract, Boswellia Serrata Extract, Carbomer, Dimethyl Sulfoxide, Ethylhexylglycerin, Eucalyptus Globulus Leaf Oil, Methylsulfonylmethane, Phenoxyethanol, Prunus Amygdalus Dulcis (Sweet Almond) Oil, SD Alcohol 40-B, Sorbitol, Water.

CLINICAL PHARMACOLOGY

Pharmacodynamics

Lidocaine is an amide-type local anesthetic agent. The penetration of lidocaine into intact skin after application of Diclona Gel is sufficient to produce analgesic effect, but less than the amount necessary to produce a complete sensory block. The mechanism of action of diclofenac sodium in the treatment of actinic keratoses (AK) is unknown. The contribution to efficacy of individual components of the vehicle has not been established.

Pharmacokinetics

Absorption

The amount of lidocaine systemically absorbed from Diclona Gel is directly related to both the duration of application and the surface area over which it is applied. When Diclona Gel is applied topically, diclofenac sodium is absorbed into the epidermis. The systematic bioavailability after topical application of diclofenac sodium is lower than after oral dosing.

Distribution

At concentrations produced by application of Diclona Gel, approximately 70% of the lidocaine dose is reported to be bound to plasma proteins, primarily alpha-1-acid glycoprotein. At higher plasma concentrations (1 to 4 mcg/mL of free base), the plasma protein binding of lidocaine is concentration dependent. Diclofenac sodium binds tightly to serum albumin.

Metabolism

It is not known if Diclona Gel is metabolized in the skin. Metabolism of diclofenac sodium following topical administration is thought to be similar to that after oral administration. The small amounts of diclofenac sodium and its metabolites appearing in the plasma following topical administration makes the quantification of specific metabolites imprecise.

Excretion

Lidocaine and its metabolites are excreted by the kidneys. Less than 10% of lidocaine is excreted unchanged. The half-life of lidocaine elimination from the plasma following IV administration is 81 to 149 minutes (mean 107 ± 22 SD, n = 15). The systemic clearance is 0.33 to 0.90 L/min (mean 0.64 ± 2 max max 0.18 SD, n = 15). Diclofenac sodium and its metabolites are excreted mainly in the urine after oral dosing.

INDICATION AND USAGE

Diclona™ is indicated for relief of pain associated with arthritis, backache, cramps, discomfort, neckache, soreness, sprains, strains. It should be applied only to intact skin. Sun avoidance is indicated during therapy.

CONTRAINDICATIONS

Diclona™ is contraindicated in patients with a known history of sensitivity to local anesthetics of the amide type, or to any other component of the product. Diclona Gel is contraindicated in patients with a known hypersensitivity to diclofenac sodium. Diclona Gel is contraindicated in patients in the setting of coronary artery bypass graft (CABG) surgery.

WARNINGS

Medicines intended to be applied to the skin should not be swallowed.

Diclona™ is flammable. Keep away from open flame.

You should never heat, microwave, or add the medicine to hot water.

Risk of Methemoglobinemia

Cases of methemoglobinemia have been reported in association with lidocaine use. Although all patients are at risk for methemoglobinemia, patients with glucose-6-phosphate dehydrogenase deficiency, congenital or idiopathic methemoglobinemia, cardiac or pulmonary compromise, infants under 6 months of age, and concurrent exposure to oxidizing agents or their metabolites are more susceptible to developing the condition. If lidocaine must be used in these patients, close monitoring for symptoms and signs of methemoglobinemia is recommended. Signs of methemoglobinemia may occur immediately or may be delayed some hours after exposure and are characterized by a cyanotic skin discoloration and/or abnormal coloration of the blood.

Methemoglobin levels may continue to rise; therefore, immediate treatment is required to avert more serious central nervous system and cardiovascular adverse effects, including seizures, coma, arrhythmias, and death.

Risk of Serious Cardiovascular Events

Cardiovascular Thrombotic Events

Nonsteroidal anti-inflammatory drugs (NSAIDs) cause an increased risk of serious cardiovascular thrombotic events, including myocardial infarction and stroke, which can be fatal. This risk may occur early in treatment and may increase with duration of use.

Fetal Toxicity

Avoid use of NSAIDs in pregnant women at about 30 weeks gestation and later. NSAIDs increase the risk of premature closure of the fetal ductus arteriosus at approximately this gestational age. Use of NSAIDs at about 20 weeks gestation or later in pregnancy may cause fetal renal dysfunction leading to oligohydramnios and, in some case, neonatal renal impairment. If NSAID treatment is necessary between about 20 weeks and 30 weeks gestation, limit Diclona Gel use to the lowest effective dose and shortest duration possible.

Serious Skin Reactions

Drug Rash with Eosinophilia and Systemic Symptoms (DRESS)

Drug Reaction with Eosinophilia and Systemic Symptoms (DRESS) has been reported in patients taking NSAIDs such as Diclona Gel. DRESS typically, although not exclusively, presents with fever, rash, lymphadenopathy, and/or facial swelling.

Heart Failure and Edema

The Coxib and traditional NSAID Trialists’ Collaboration meta-analysis of randomized controlled trials demonstrated an approximately two-fold increase in hospitalizations for heart failure in COX-2 selective-treated patients and nonselective NSAID-treated patients compared to placebo-treated patients. Avoid the use of Diclona Gel in patients with severe heart failure unless benefits are expected to outweigh the risk of worsening heart failure. If Diclona Gel is used in patients with severe heart failure, monitor patients for signs of worsening heart failure.

PRECAUTIONS

General

Diclona™ should be used with caution in patients with active gastrointestinal ulceration or bleeding and severe renal or hepatic impairments. Diclona Gel should not be applied to open skin wounds, infections, or exfoliative dermatitis.

Hepatic Disease

Patients with severe hepatic disease are at greater risk of developing toxic blood concentrations of lidocaine, because of their inability to metabolize lidocaine normally.

Allergic Reactions

Patients allergic to para-aminobenzoic acid derivatives (procaine, tetracaine, benzocaine, etc.) have not shown cross sensitivity to lidocaine. However, Diclona Gel should be used with caution in patients with a history of drug sensitivities, especially if the etiologic agent is uncertain.

Non-intact Skin

Application to broken or inflamed skin, although not tested, may result in higher blood concentrations of lidocaine from increased absorption. Diclona Gel is only recommended for use on intact skin.

External Heat Sources

Placement of external heat sources, such as heating pads or electric blankets, over Diclona Gel is not recommended as this has not been evaluated and may increase plasma lidocaine levels.

Eye Exposure

The contact of Diclona Gel with eyes, although not studied, should be avoided based on the findings of severe eye irritation with the use of similar products in animals. If eye contact occurs, immediately wash out the eye with water or saline and protect the eye until sensation returns.

Information for Patients Methemoglobinemia

Inform patients that use of local anesthetics may cause methemoglobinemia, a serious condition that must be treated promptly. Advise patients or caregivers to stop use and seek immediate medical attention if they or someone in their care experience the following signs or symptoms: pale, gray, or blue colored skin (cyanosis); headache; rapid heart rate; shortness of breath; lightheadedness; or fatigue.

Drug Interactions

Specific interaction studies between Diclona Gel and other topical or oral agents were not performed.

Oral Nonsteroidal Anti-Inflammatory Drugs

Although low, there is systemic exposure to diclofenac sodium following labeled use of Diclona Gel. Therefore, concomitant administration of Diclona Gel with oral NSAIDs or aspirin may result in increased NSAID adverse effects.

Antiarrhythmic Drugs

Diclona Gel should be used with caution in patients receiving Class I antiarrhythmic drugs (such as tocainide and mexiletine) since the toxic effects are additive and potentially synergistic.

Local Anesthetics

When Diclona Gel is used concomitantly with other products containing local anesthetic agents, the amount absorbed from all formulations must be considered.

Drugs That May Cause Methemoglobinemia When Used with Diclona Gel

Patients who are administered local anesthetics are at increased risk of developing methemoglobinemia when concurrently exposed to the following drugs, which could include other local anesthetics:

Examples of Drugs Associated with Methemoglobinemia:

Class Examples

Nitrates/Nitrites nitric oxide, nitroglycerin, nitroprusside, nitrous oxide Local anesthetics

articaine, benzocaine, bupivacaine, lidocaine, mepivacaine, prilocaine, procaine, ropivacaine, tetracaine

Antineoplastic agents cyclophosphamide, flutamide, hydroxyurea, ifosfamide, rasburicase, antibiotics dapsone, nitrofurantoin, para-aminosalicylic acid, sulfonamides, antimalarials chloroquine, primaquine anticonvulsants, phenobarbital, phenytoin, sodium valproate, opher drugs acetaminophen, metoclopramide, quinine, sulfasalazine carcinogenesis, mutagenesis.

Impairment of Fertility

The effect of Diclona Gel on fertility has not been studied.

Pregnancy

Teratogenic Effects

Pregnancy Category B.

Diclona Gel has not been studied in pregnancy.

Labor and Delivery

Diclona Gel has not been studied in labor and delivery.

Nursing Mothers

Diclona Gel has not been studied in nursing mothers.

Pediatric Use

Safety and effectiveness in pediatric patients have not been established.

Geriatric Use

Reported clinical experience has not identified differences in responses between the elderly and younger patients, but greater sensitivity of some older individuals cannot be ruled out.

ADVERSE REACTIONS

Application Site Reactions

During or immediately after treatment with Diclona™, the skin at the site of application may develop blisters, bruising, burning sensation, depigmentation, dermatitis, discoloration, edema, erythema, exfoliation, irritation, papules, petechia, pruritus, vesicles, or may be the locus of abnormal sensation. These reactions are generally mild and transient, resolving spontaneously within a few minutes to hours.

Other Adverse Events

Due to the nature and limitation of spontaneous reports in post marketing surveillance, causality has not been established for additional reported adverse events including:

Asthenia, confusion, disorientation, dizziness, headache, hyperesthesia, hypoesthesia, lightheadedness, metallic taste, nausea, nervousness, pain exacerbated, paresthesia, somnolence, taste alteration, vomiting, visual disturbances such as blurred vision, flushing, tinnitus, and tremor.

Systemic (Dose-Related) Reactions

Systemic adverse reactions following appropriate use of Diclona™ are unlikely, due to the small dose absorbed (see CLINICAL PHARMACOLOGY, Pharmacokinetics). Systemic adverse effects of lidocaine is similar in nature to those observed with other amide local anesthetic agents, including CNS excitation and/or depression (light headedness, nervousness, apprehension, euphoria, confusion, dizziness, drowsiness, tinnitus, blurred or double vision, vomiting, sensations of heat, cold or numbness, twitching, tremors, convulsions, unconsciousness, respiratory depression and arrest). Excitatory CNS reactions may be brief or not occur at all, in which case the first manifestation may be drowsiness merging into unconsciousness. Cardiovascular manifestations may include bradycardia, hypotension and cardiovascular collapse leading to arrest.

OVERDOSAGE

Lidocaine overdose from cutaneous absorption is rare but could occur. Excessive dosing by applying Diclona Gel to larger areas could result in increased absorption of lidocaine and high blood concentrations, leading to serious adverse effects (see ADVERSE REACTIONS, Systemic Reactions). Longer duration of application of more than the recommended number of doses, smaller patients, or impaired elimination may all contribute to increased blood concentration of lidocaine. Due to the low systemic absorption of topically-applied diclofenac sodium, overdosage of diclofenac sodium is unlikely.

DOSAGE AND ADMINISTRATION

Apply Diclona™ to intact skin to cover the most painful area. Clean and dry the affected area. Apply product directly to your skin, up to 4 times daily. Clothing may be worn over the area of application.

If irritation or a burning sensation occurs during application, wash the product off your skin and do not reapply until the irritation subsides.

When Diclona™ is used concomitantly with other products containing local anesthetic agents, the amount absorbed from all formulations must be considered.

HANDLING AND DISPOSAL

Hands should be washed after the handling of Diclona Gel, and eye contact with Diclona Gel should be avoided. Store in a cool, dry place with lid tightly closed.

Diclona™ should be kept out of the reach of children.

HOW SUPPLIED

Diclona™ is available as the following:

1 tube, 3.5oz

NDC 83881-102-35

Store at 25°C (77°F); excursions permitted to 15°-30°C (59°-86°F). [See USP Controlled Room Temperature].

For more information, contact Clinic Pharma, info@clinicpharma.com

Manufactured for:

Clinic Pharma | Las Vegas, NV 89121

MADE IN U.S.A

Relabeled By Preferred Pharmaceuticals Inc.